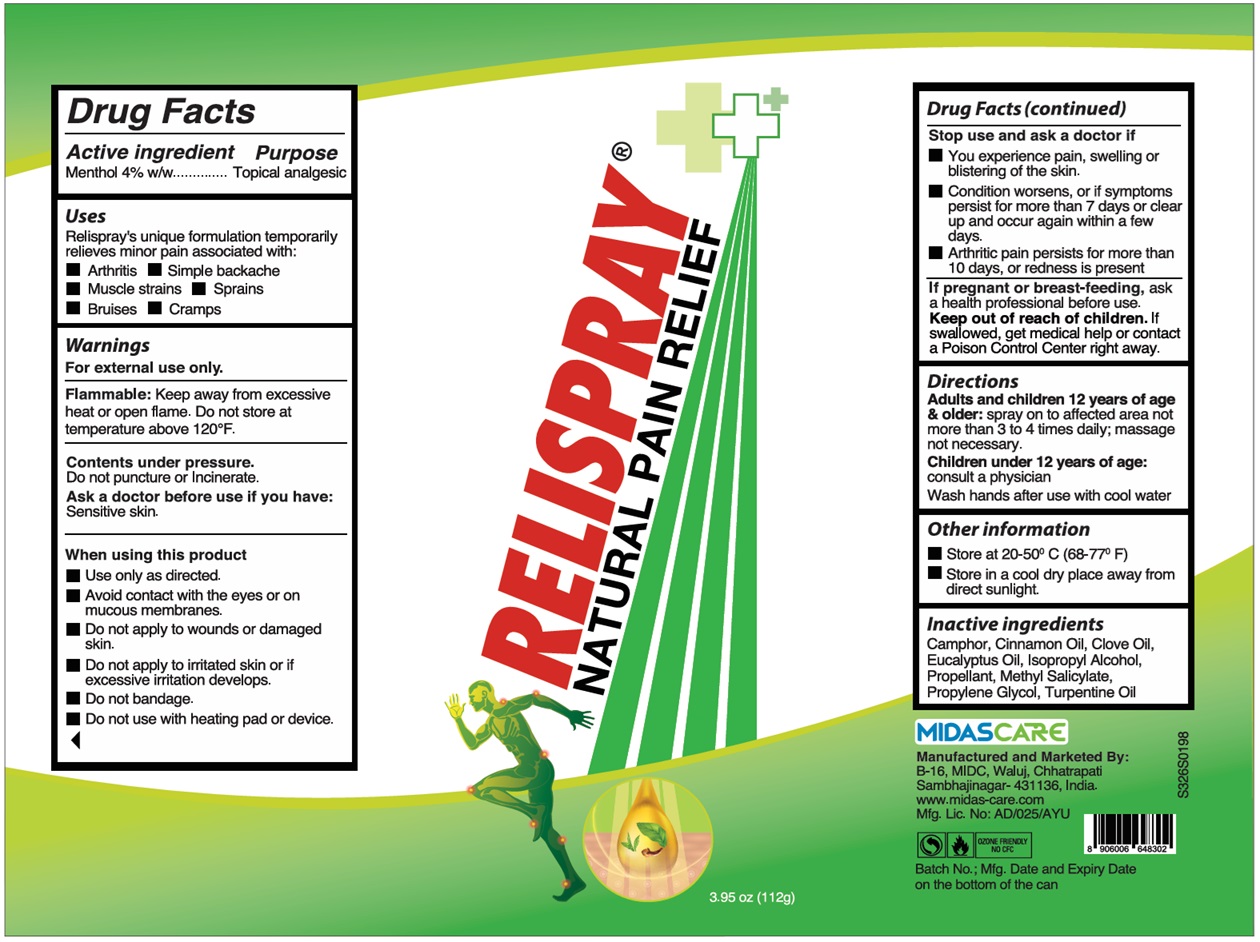 DRUG LABEL: RELISPRAY NATURAL PAIN RELIEF
NDC: 46063-101 | Form: AEROSOL, SPRAY
Manufacturer: Midas-Care Pharmaceuticals, Pvt. Ltd
Category: otc | Type: HUMAN OTC DRUG LABEL
Date: 20251030

ACTIVE INGREDIENTS: MENTHOL, UNSPECIFIED FORM 4 g/100 g
INACTIVE INGREDIENTS: CAMPHOR (NATURAL); CINNAMON OIL; CLOVE OIL; EUCALYPTUS OIL; ISOPROPYL ALCOHOL; LIQUEFIED PETROLEUM GAS; METHYL SALICYLATE; PROPYLENE GLYCOL; TURPENTINE OIL

RELISPRAY® NATURAL PAIN RELIEF

Active ingredient

Menthol 4% w/w

Purpose

Topical analgesic

Uses

Relispray's unique formulation temporarily relieves minor pain associated with:
• Arthritis • Simple backache
• Muscle strains • Sprains
• Bruises • Cramps

Warnings

For external use only.

Flammable: Keep away from excessive heat or open flame. Do not store at temperature above 120°F.

Contents under pressure.
Do not puncture or Incinerate.

Ask a doctor before use if you have: Sensitive skin.

When using this product
• Use only as directed.
• Avoid contact with the eyes or on mucous membranes.
• Do not apply to wounds or damaged skin.
• Do not apply to irritated skin or if excessive irritation develops.
• Do not bandage.
• Do not use with heating pad or device.

Stop use and ask a doctor if
• You experience pain, swelling or blistering of the skin.
• Condition worsens, or if symptoms persist for more than 7 days or clear up and occur again within a few days.
• Arthritic pain persists for more than 10 days, or redness is present

If pregnant or breast-feeding, ask a health professional before use.

Keep out of reach of children. If swallowed, get medical help or contact a Poison Control Center right away.

Directions

Adults and children 12 years of age & older: spray on to affected area not more than 3 to 4 times daily; massage not necessary.

Children under 12 years of age: consult a physician

Wash hands after use with cool water

Other information

• Store at 20-50° C (68-77° F)
• Store in a cool dry place away from direct sunlight.

Inactive ingredients

Camphor, Cinnamon Oil, Clove Oil, Eucalyptus Oil, Isopropyl Alcohol, Propellant, Methyl Salicylate, Propylene Glycol, Turpentine Oil

MIDASCARE
Manufactured and Marketed By:
B-16, MIDC, Waluj, Chhatrapati
Sambhajinagar- 431136, India.
www.midas-care.com

OZONE FRIENDLY
NO CFC